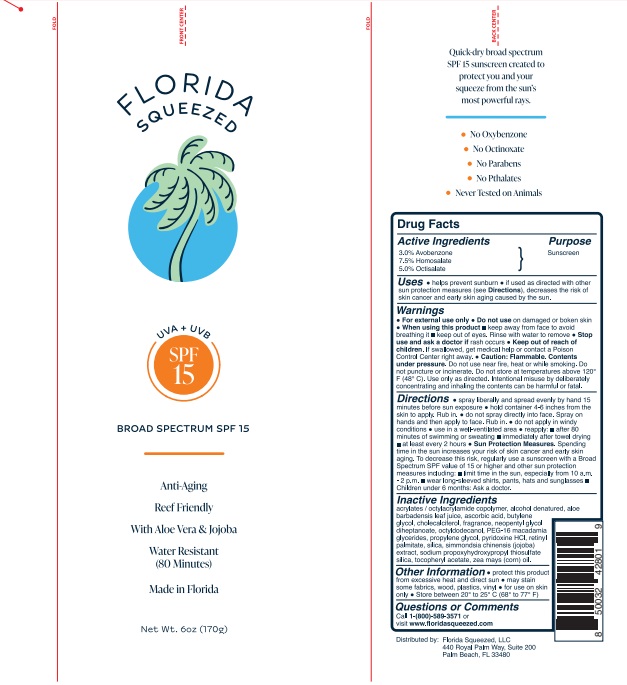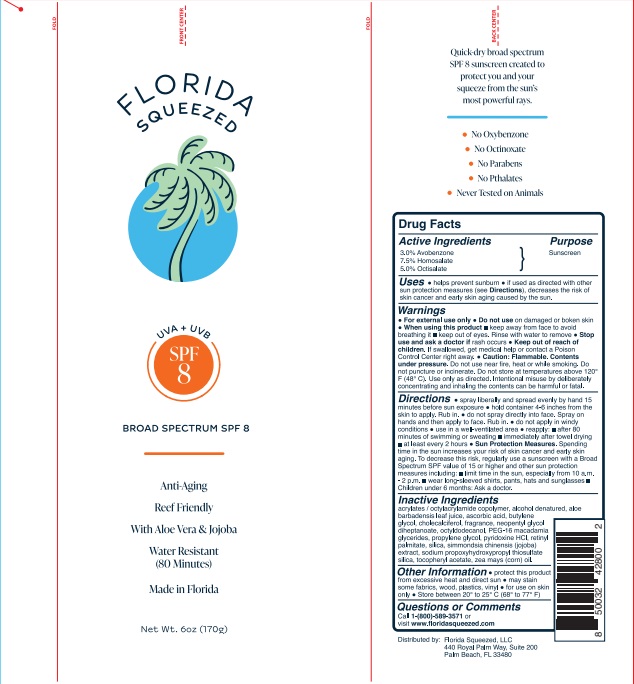 DRUG LABEL: Florida Squeeze SPF 15
NDC: 73440-2801 | Form: SPRAY
Manufacturer: Cross Brands Contract Filling
Category: otc | Type: HUMAN OTC DRUG LABEL
Date: 20220805

ACTIVE INGREDIENTS: AVOBENZONE 5.1 g/170 g; OCTISALATE 8.5 g/170 g; HOMOSALATE 12.75 g/170 g
INACTIVE INGREDIENTS: ALCOHOL 129.71 g/170 g

Florida Squeezed SPF 15